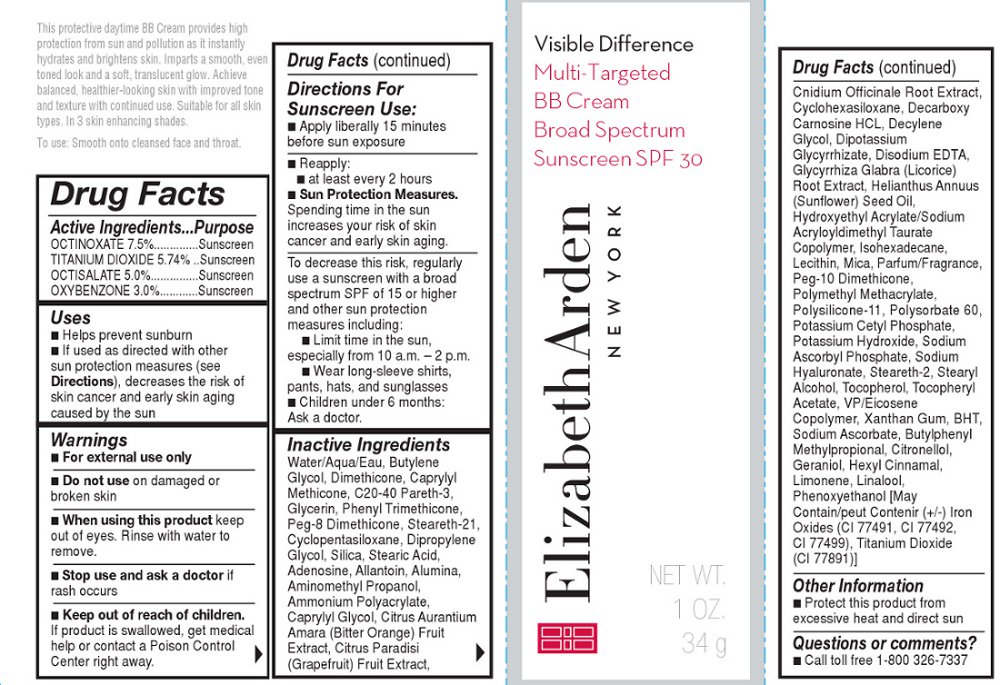 DRUG LABEL: VISIBLE DIFFERENCE MULTI TARGETED BB CREAM BROAD SPECTRUM SUNSCREEN SPF 30 SHADE 3
NDC: 67938-2004 | Form: CREAM
Manufacturer: Elizabeth Arden, Inc
Category: otc | Type: HUMAN OTC DRUG LABEL
Date: 20130731

ACTIVE INGREDIENTS: OCTINOXATE 2.55 g/34 g; TITANIUM DIOXIDE 1.95 g/34 g; OCTISALATE 1.7 g/34 g; OXYBENZONE 1.02 g/34 g
INACTIVE INGREDIENTS: WATER; BUTYLENE GLYCOL; DIMETHICONE; C20-40 PARETH-3; GLYCERIN; PHENYL TRIMETHICONE; PEG-8 DIMETHICONE; STEARETH-21; DIPROPYLENE GLYCOL; STEARIC ACID; ADENOSINE; ALLANTOIN; CAPRYLYL GLYCOL; DECYLENE GLYCOL; HYDROXYETHYL ACRYLATE/SODIUM ACRYLOYLDIMETHYL TAURATE COPOLYMER (45000 MPA.S AT 1%); ISOHEXADECANE; LECITHIN, SOYBEAN; MICA; PEG-10 DIMETHICONE (600 CST); POLYSORBATE 60; POTASSIUM CETYL PHOSPHATE; POTASSIUM HYDROXIDE; SODIUM ASCORBYL PHOSPHATE; STEARETH-2; STEARYL ALCOHOL; TOCOPHEROL; XANTHAN GUM; SODIUM ASCORBATE; BUTYLPHENYL METHYLPROPIONAL; GERANIOL; PHENOXYETHANOL

222616

DESCRIPTION

This protective daytime BB Cream provides high protection from sun and pollution as it instantly hydrates and brightens skin. Imparts a smooth, even toned look and a soft, translucent glow.

INDICATIONS AND USAGE

Smooth onto cleansed face and throat.

WARNINGS

For external use only

OTC ACTIVE INGREDIENT

OCTINOXATE 7.5%..............Sunscreen

TITANIUM DIOXIDE 5.74% ..Sunscreen

OCTISALATE 5.0%...............Sunscreen

OXYBENZONE 3.0%............Sunscreen

INACTIVE INGREDIENT

Water/Aqua/Eau, Butylene Glycol, Dimethicone, Caprylyl Methicone, C20-40 Pareth-3, Glycerin, Phenyl Trimethicone, Peg-8 Dimethicone, Steareth-21, Cyclopentasiloxane, Dipropylene Glycol, Silica, Stearic Acid, Adenosine, Allantoin, Alumina, Aminomethyl Propanol, Ammonium Polyacrylate, Caprylyl Glycol, Citrus Aurantium Amara (Bitter Orange) Fruit Extract, Citrus Paradisi (Grapefruit) Fruit Extract, Cnidium Officinale Root Extract, Cyclohexasiloxane, Decarboxy Carnosine HCL, Decylene Glycol, Dipotassium Glycyrrhizate, Disodium EDTA, Glycyrrhiza Glabra (Licorice) Root Extract, Helianthus Annuus (Sunflower) Seed Oil, Hydroxyethyl Acrylate/Sodium Acryloyldimethyl Taurate Copolymer, Isohexadecane, Lecithin, Mica, Parfum/Fragrance, Peg-10 Dimethicone, Polymethyl Methacrylate, Polysilicone-11, Polysorbate 60, Potassium Cetyl Phosphate, Potassium Hydroxide, Sodium Ascorbyl Phosphate, Sodium Hyaluronate, Steareth-2, Stearyl Alcohol, Tocopherol, Tocopheryl Acetate, VP/Eicosene Copolymer, Xanthan Gum, BHT, Sodium Ascorbate, Butylphenyl Methylpropional, Citronellol, Geraniol, Hexyl Cinnamal, Limonene, Linalool, Phenoxyethanol [May Contain/peut Contenir (+/-) Iron Oxides (CI 77491, CI 77492, CI 77499), Titanium Dioxide (CI 77891)]

DOSAGE AND ADMINISTRATION

Smooth onto face and throat

OTC - KEEP OUT OF REACH OF CHILDREN

Keep out of reach of children.

OTC - PURPOSE

Provides SPF 30 sun protection

OTC - WHEN USING

Keep out of eyes. Rinse with water to remove

DO NOT USE

on damaged or broken skin

STOP USE

If rash occurs